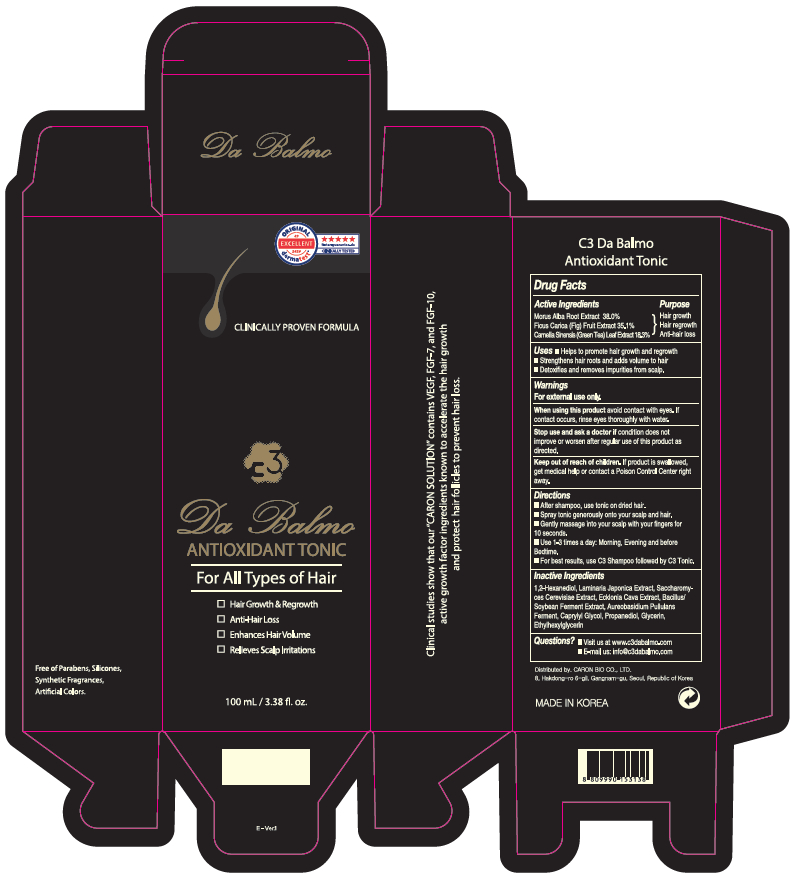 DRUG LABEL: C3 Da Balmo Antioxidant
NDC: 73862-302 | Form: SPRAY
Manufacturer: E.CIS COSMETIC.,Co.Ltd
Category: homeopathic | Type: HUMAN OTC DRUG LABEL
Date: 20210416

ACTIVE INGREDIENTS: CAMELLIA SINENSIS ROOT 18.3 mg/1 mL; MORUS ALBA ROOT 38 mg/1 mL; FICUS CARICA WHOLE 35.1 mg/1 mL
INACTIVE INGREDIENTS: CAPRYLYL GLYCOL; PROPANEDIOL; GLYCERIN; ETHYLHEXYLGLYCERIN; 1,2-HEXANEDIOL; LAMINARIA JAPONICA; SACCHAROMYCES CEREVISIAE; ECKLONIA CAVA

C3 Da Balmo Tonic

Active Ingredient

Morus Alba Root Extract 38.0%
Ficus Carica (Fig) Fruit Extract 35.1%
Camellia Sinensis (Green Tea) Leaf Extract 18.3%

Purpose

- Hair growth
- Hair regrowth
- Anti-hair loss

Uses

- Helps to promotes hair growth and regrowth
- Strengthens hair root and adds volume to hair
- Detoxifies and removes impurities from scalp

Warnings

For external use only.

When using this product avoid contact with eyes. If contact occurs, rinse eyes thoroughly with water.

Stop use and ask a doctor if condition does not improve or worsen after regular use of this product as directed

Keep out of reach of children. If product is swallowed, get medical help or contact a Poison Control Center right away.

Directions

- After shampoo, use tonic on dried hair.
- Spray tonic generously onto your scalp and hair.
- Gently massage into your scalp with your fingers for 10 seconds.
- Use 1-3 times a day: Morning, Evening and before Bedtime.
- For best results, use C3 Shampoo followed by C3 Tonic.

Inactive ingredients

1,2-Hexanediol, Laminaria Japonica Extract, Saccharomyces Cerevisiae Extract, Ecklonia Cava Extract, Bacillus/Soybean Ferment Extract, Aureobasidium Pullulans Ferment, Caprylyl Glycol, Propanediol, Glycerin, Ethylhexylglycerin

Qustions?

- Visit us at www.c3dabalmo.com
- E-mail us: info@c3dabalmo.com

Principal Display Panel

Original Excellent dermatest
5-star-guarantee.de Clinically Tested

Clinically Proven Formula

C3
Da Balmo

Antioxidant Tonic

For All Types of Hair

- Hair Growth & Regrowth
- Anti-Hair Loss
- Enhances Hair Volume
- Relieves Scalp Irritations

100 mL / 3.38 fl. oz.

Distributed by: Caron Bio Co., Ltd.
8 Hakdong-ro, 6-gil, Gangnam-gu, Seoul, Republic of Korea

Made in Korea